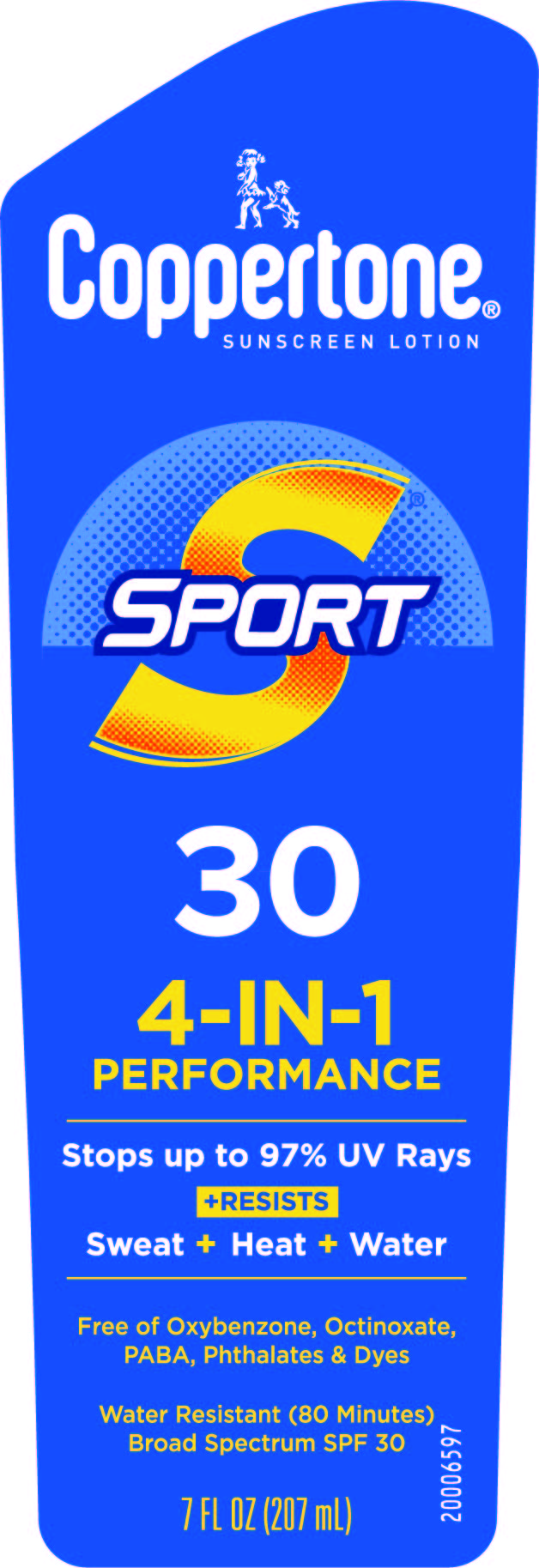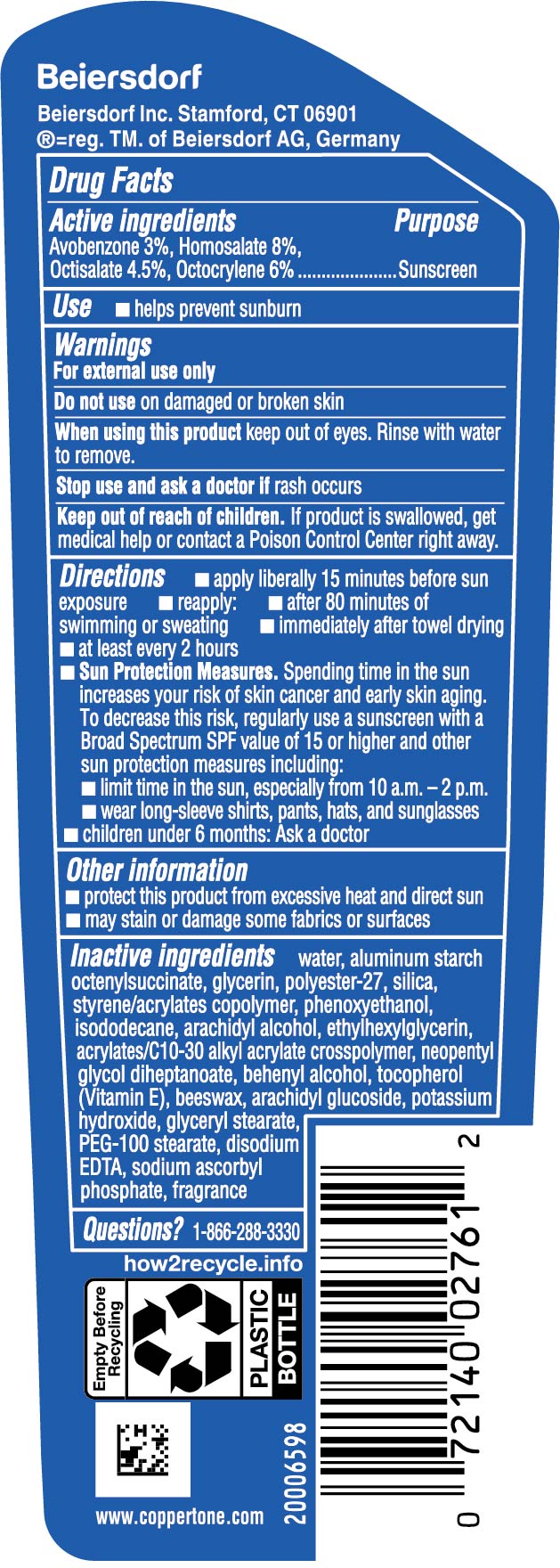 DRUG LABEL: Coppertone Sport Sunscreen SPF 30
NDC: 66800-2669 | Form: LOTION
Manufacturer: Beiersdorf Inc
Category: otc | Type: HUMAN OTC DRUG LABEL
Date: 20251231

ACTIVE INGREDIENTS: AVOBENZONE 3 g/100 g; HOMOSALATE 8 g/100 g; OCTOCRYLENE 6 g/100 g; OCTISALATE 4.5 g/100 g
INACTIVE INGREDIENTS: PEG-20 STEARATE; STYRENE/ACRYLAMIDE COPOLYMER (MW 500000); ARACHIDYL ALCOHOL; SILICON DIOXIDE; ALUMINUM STARCH OCTENYLSUCCINATE; NEOPENTYL GLYCOL DIHEPTANOATE; POTASSIUM HYDROXIDE; DOCOSANOL; TOCOPHEROL; GLYCERYL STEARATE SE; WATER; GLYCERIN; POLYESTER-7; DISODIUM EDTA-COPPER; SODIUM ASCORBYL PHOSPHATE; FRAGRANCE FLORAL ORC0902236; SYNTHETIC BEESWAX; ARACHIDYL GLUCOSIDE; PHENOXYETHANOL; ISODODECANE; ETHYLHEXYLGLYCERIN; CARBOMER INTERPOLYMER TYPE A (55000 CPS)

Sport Lotion SPF 30

Active ingredients

Avobenzone 3%, Homosalate 8%, Octisalate 4.5%, Octocrylene 6%

Purpose

Sunscreen

Use

■ helps prevent sunburn

Warnings

For external use only

Do not useon damaged or broken skin

WHEN USING

When using this productkeep out of eyes. Rinse with water to remove.

Stop use and ask a doctor ifrash occurs

Keep out of reach of children.If product is swallowed, get medical help or contact a Poison Control Center right away.

Directions

■ apply liberally 15 minutes before sun exposure

■ reapply:

■ after 80 minutes of swimming or sweating

■ immediately after towel drying

■ at least every 2 hours

■ Sun Protection Measures.Spending time in the sun increases your risk of skin cancer and early skin aging. To decrease this risk, regularly use a sunscreen with a Broad Spectrum SPF value of 15 or higher and other sun protection measures including:

■ limit time in the sun, especially from 10 a.m. – 2 p.m.

■ wear long-sleeve shirts, pants, hats, and sunglasses

■ children under 6 months: Ask a doctor

Other information

■ protect this product from excessive heat and direct sun

■ may stain or damage some fabrics or surfaces

Inactive ingredients

water, aluminum starch octenylsuccinate, glycerin, polyester-27, silica, styrene/acrylates copolymer, phenoxyethanol, isododecane, arachidyl alcohol, ethylhexylglycerin, acrylates/C10-30 alkyl acrylate crosspolymer, neopentyl glycol diheptanoate, behenyl alcohol, tocopherol (Vitamin E), beeswax, arachidyl glucoside, potassium hydroxide, glyceryl stearate, PEG-100 stearate, disodium EDTA, sodium ascorbyl phosphate, fragrance

Questions?

1-866-288-3330

PACKAGE LABEL

Coppertone®Sunscreen Lotion

Sport 30

4-IN-1 Performance

Stops up to 97% UV Rays

+Resists

Sweat+Heat+Water

Free of Oxybenzone, Octinoxate, PABA, Phthalates & Dyes

Water Resistant (80 Minutes)

Broad Spectrum SPF 30